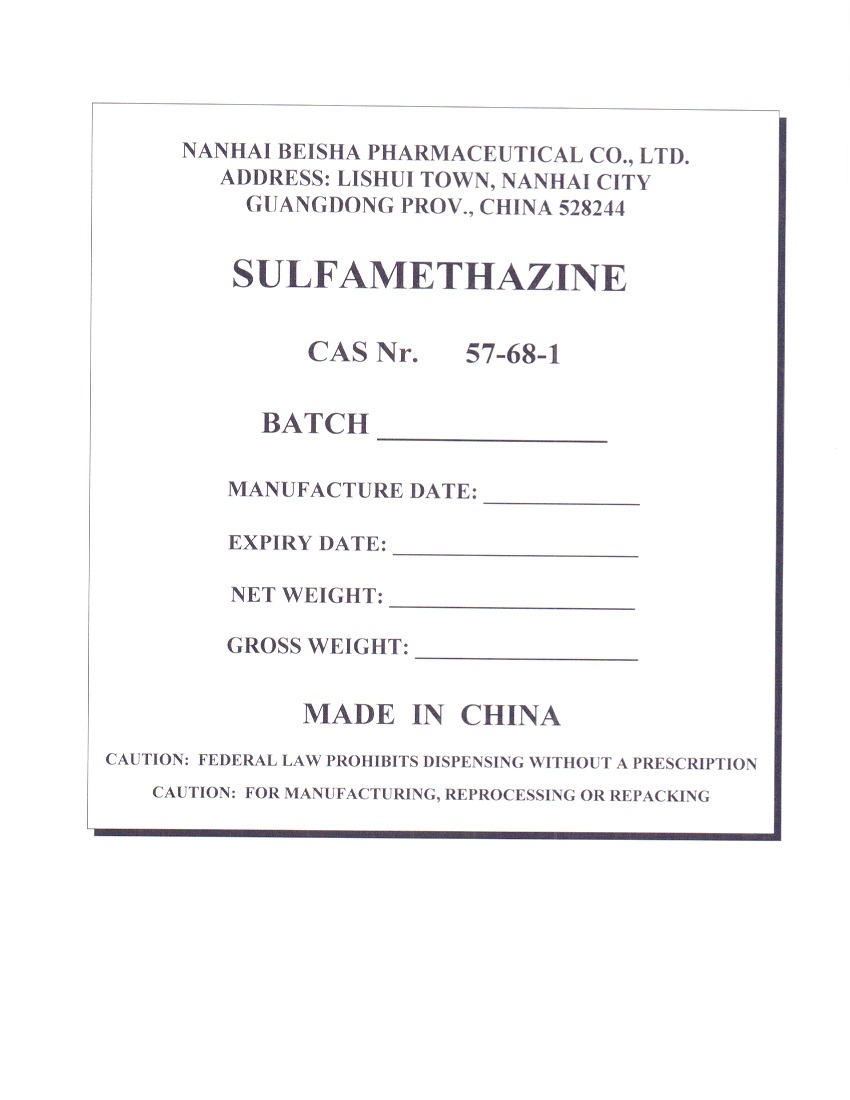 DRUG LABEL: SULFAMETHAZINE
NDC: 63422-701 | Form: POWDER
Manufacturer: NANHAI BEISHA PHARMACEUTICAL CO., LTD.
Category: other | Type: BULK INGREDIENT - ANIMAL DRUG
Date: 20250806

ACTIVE INGREDIENTS: SULFAMETHAZINE 25 kg/25 kg

PACKAGE LABEL

Add image transcription here...